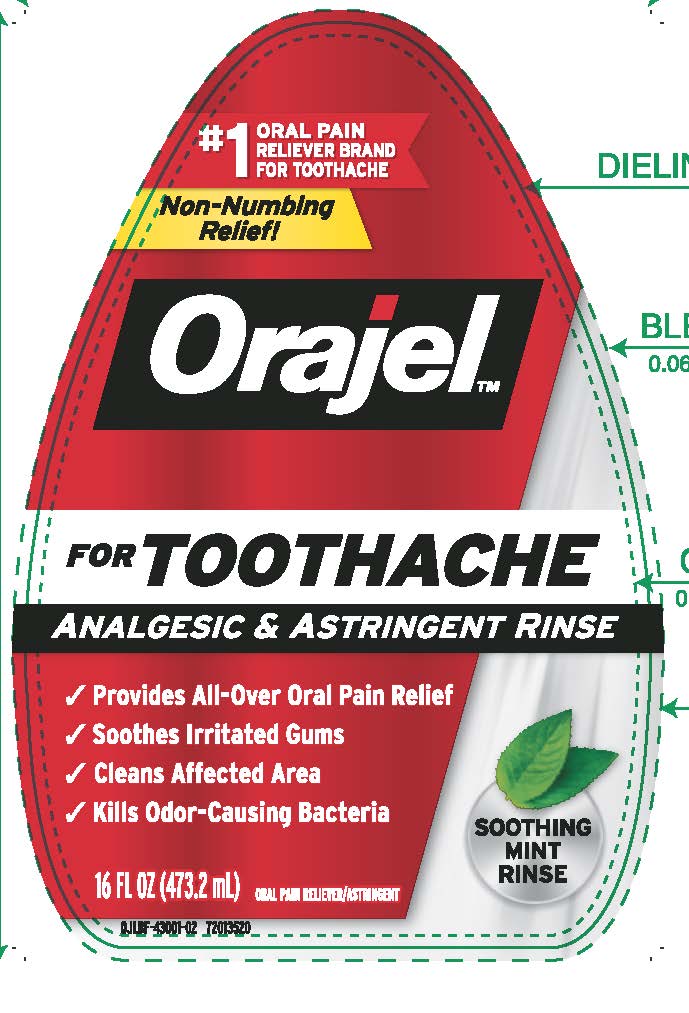 DRUG LABEL: Orajel Toothache Rinse
NDC: 10237-764 | Form: LIQUID
Manufacturer: Church & Dwight Co., Inc.
Category: otc | Type: HUMAN OTC DRUG LABEL
Date: 20241127

ACTIVE INGREDIENTS: BENZYL ALCOHOL 2.7 mg/1 mL; ZINC CHLORIDE 1.5 mg/1 mL
INACTIVE INGREDIENTS: METHYL SALICYLATE; POLOXAMER 338; POLYSORBATE 20; SODIUM BENZOATE; SORBITOL; FD&C BLUE NO. 1; CALCIUM DISODIUM PYROPHOSPHATE; MENTHOL, UNSPECIFIED FORM; POTASSIUM SODIUM SACCHARATE; SODIUM PYROPHOSPHATE; WATER; ALCOHOL

Orajel Toothache Rinse

ACTIVE INGREDIENT

Benzyl Alcohol 0.27%

Zinc Chloride 0.15%

PURPOSE

Oral pain reliever

Oral astringent

INDICATIONS AND USAGE

Usefor temporary relief of pain due to toothaches, minor irritation of the mouth and gums, occasional minor irritation, pain, sore mouth and sore throat

Warnings

Do not usethis product for more than 7 days unless directed by a dentist or healthcare provider

When using this product• do not swallow • do not exceed recommended dosage

Stop use and see your physician promptly if• swelling, rash or fever develops • irritation, pain or redness persists or worsens • sore mouth symptoms do not improve in 7 days • allergic reaction occurs • sore thoat is severe, persists for more than 2 days, is accompanied or followed by fever, headache, rash, nausea, or vomiting.

Keep out of reach of children.If more than used for rinsing is accidentally swallowed, get medical help or contact a Poison Control Center right away

Directions

•remove imprinted safety seal from bottle cap

• to remove child-resistant cap, squeeze smooth sides of cap while turning. Reclose tightly. Ready to use, no mixing needed.

Adults and children 2 years of age or over:

Swish one-half capful (2 teaspoons = 10mL) around the mouth over the affected area for at least 1 minute and then spit out. Use up to 4 times daily after meals and at bedtime or as directed by a dentist or healthcare provider

Children under 12 years of age:

Should be supervised in the use of this product

Children under 2 years of age:

Consult a dentist or healthcare provider

Other Information •cap tightly • keep away from heat or direct sunlight • do not use if safety seal is broken or missing

INACTIVE INGREDIENT

Inactive Ingredientsalcohol (4.1% by volume), blue 1, disodium pyrophosphate, menthol, methyl salicylate, poloxamer 338, polysorbate 20, sodium benzoate, sodium saccharin, sorbitol, tetrasodium pyrophosphate, water

QUESTIONS

Questions or commentscalls us at 800 952 5080 Monday through Friday 9 to 5 ET or visit our website at www orajel com

PACKAGE LABEL

#1

ORAL PAIN RELIEVER

BRAND FOR TOOTHACHE

NON-NUMBING RELIEF!

Orajel™

For TOOTHACHE

Analgesic & Astringent Rinse

Provides All-Over Oral Pain Relief

Soothes Irritated Gums

Cleans Affected Area

Kills Odor-Causing Bacteria

Soothing

Mint

Rinse

ORAL PAIN RELIEVER/

ASTRINGENT

16 FL OZ (473.2 mL)